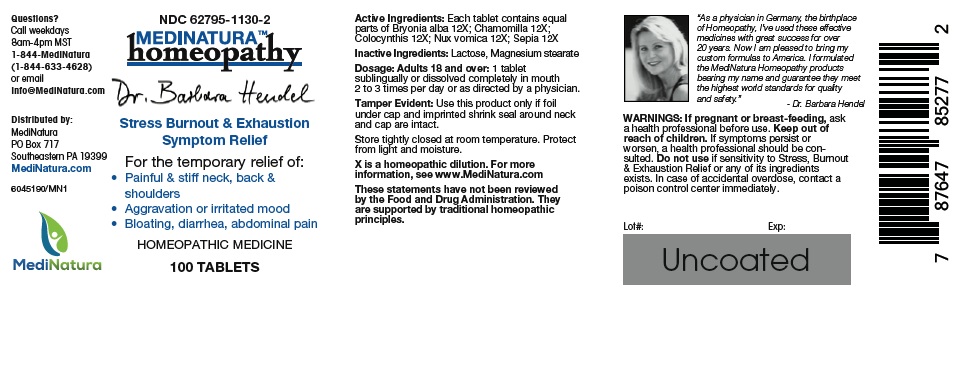 DRUG LABEL: Hendel Stress, Burnout and Exhaustion Symptoms
NDC: 62795-1130 | Form: TABLET
Manufacturer: MediNatura Inc
Category: homeopathic | Type: HUMAN OTC DRUG LABEL
Date: 20181018

ACTIVE INGREDIENTS: BRYONIA ALBA ROOT 12 [hp_X]/1 1; MATRICARIA CHAMOMILLA 12 [hp_X]/1 1; CITRULLUS COLOCYNTHIS FRUIT PULP 12 [hp_X]/1 1; STRYCHNOS NUX-VOMICA SEED 12 [hp_X]/1 1; SEPIA OFFICINALIS JUICE 12 [hp_X]/1 1
INACTIVE INGREDIENTS: LACTOSE, UNSPECIFIED FORM; Magnesium stearate

Hendel Stress, Burnout and Exhaustion Symptoms

WARNINGS

If pregnant or breast-feeding, ask a health professional before use. Keep out of reach of children. If symptoms persist or worsen, a health professional should be consulted. Do not use if sensitivity to Stress, Burnout & Exhaustion Relief or any of its ingredients exists. In case of accidental overdose, contact a Poison Control Center immediately.

KEEP OUT OF REACH OF CHILDREN

INDICATIONS

Stress, Burnout & Exhaustion Relief

ACTIVE INGREDIENT

Aesculus hippocastanum 6X; Bryonia 6X; Colocynthis 6X; Dulcamara 6X; Gnaphalium polycephalum 6X; Hypericum perforatum 6X; Nux vomica 6X; Rhus tox 12X

INACTIVE INGREDIENT

Lactose, Magnesium stearate

DIRECTIONS

Adults 18 and over: 1 tablet sublingually or dissolved completely in mouth 2 to 3 times per day or as directed by a physician

USES

: For the temporary relief of:
• Painful & stiff neck, back & shoulders
• Aggravation or irritated mood
• Bloating, diarrhea, abdominal pain.